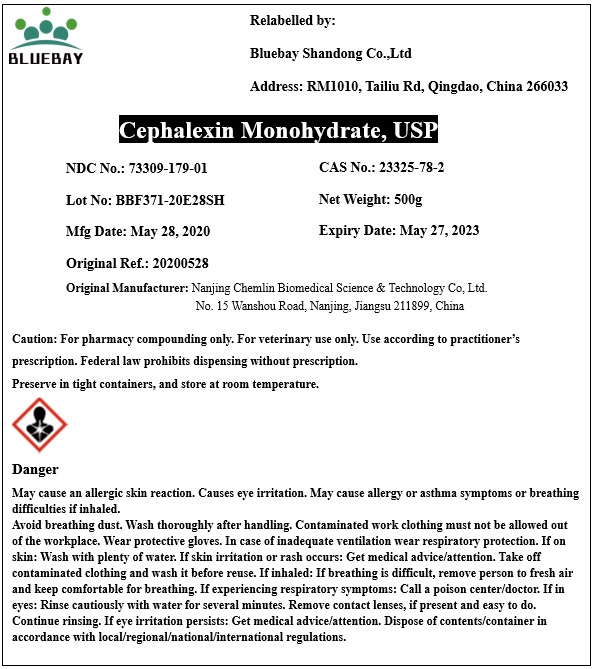 DRUG LABEL: Cephalexin monohydrate
NDC: 73309-179 | Form: POWDER
Manufacturer: BLUEBAY SHANDONG CO.,LTD
Category: other | Type: BULK INGREDIENT
Date: 20200820

ACTIVE INGREDIENTS: CEPHALEXIN 1 g/1 g

Cephalexin monohydrate